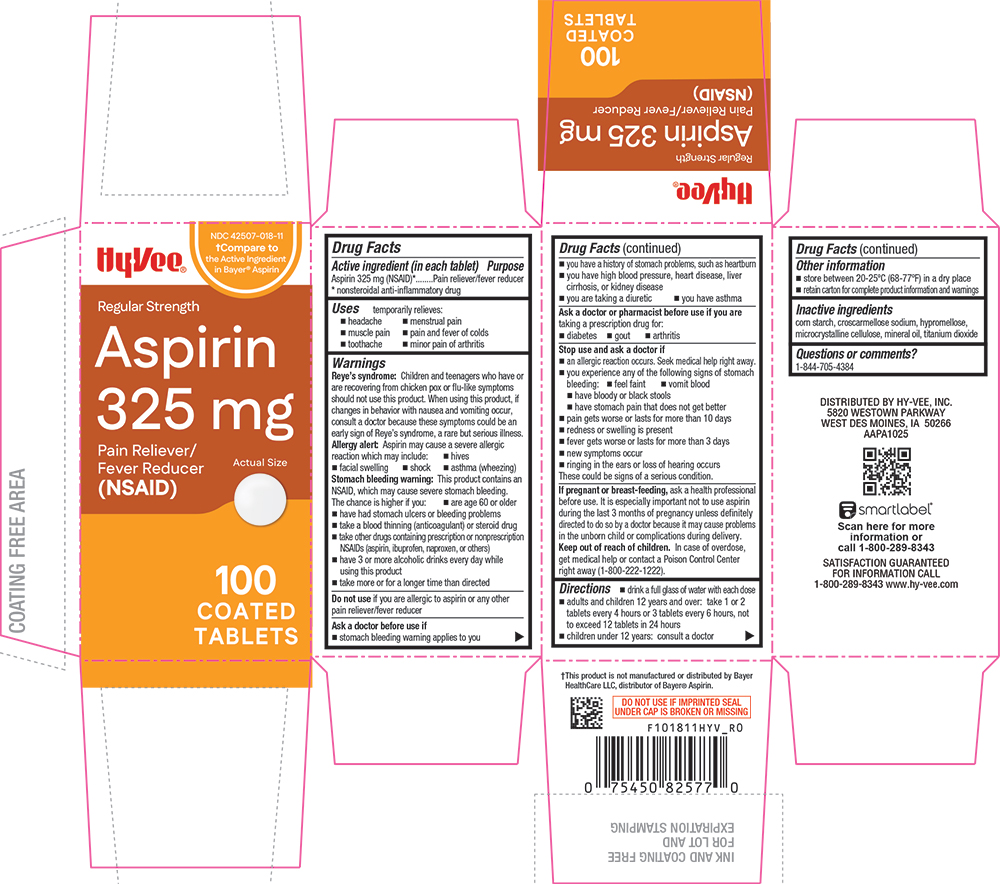 DRUG LABEL: ASPIRIN 325 mg
NDC: 42507-018 | Form: TABLET, COATED
Manufacturer: HYVEE INC
Category: otc | Type: HUMAN OTC DRUG LABEL
Date: 20260113

ACTIVE INGREDIENTS: ASPIRIN 325 mg/1 1
INACTIVE INGREDIENTS: CROSCARMELLOSE SODIUM; HYPROMELLOSES; CELLULOSE, MICROCRYSTALLINE; MINERAL OIL; STARCH, CORN; TITANIUM DIOXIDE

1018-HYV-2026-0113

Drug Facts

Active ingredient (in each tablet)

Aspirin 325 mg (NSAID)*

* nonsteroidal anti-inflammatory drug

Purpose

Pain reliever/fever reducer

Uses

temporarily relieves:

- headache
- muscle pain
- toothache
- menstrual pain
- pain and fever of colds
- minor pain of arthritis

Warnings

Reye's syndrome

Children and teenagers who have or are recovering from chicken pox or flu-like symptoms should not use this product. When using this product, if changes in behavior with nausea and vomiting occur, consult a doctor because these symptoms could be an early sign of Reye's syndrome, a rare but serious illness.

Allergy alert

Aspirin may cause a severe allergic reaction which may include:

- hives
- facial swelling
- asthma (wheezing)
- shock

Stomach bleeding warning

This product contains an NSAID, which may cause severe stomach bleeding.

The chance is higher if you:

- are age 60 or older
- have had stomach ulcers or bleeding problems
- take a blood thinning (anticoagulant) or steroid drug
- take other drugs containing prescription or nonprescription NSAIDs (aspirin, ibuprofen, naproxen, or others)
- have 3 or more alcoholic drinks every day while using this product
- take more or for a longer time than directed

DO NOT USE

Do not useif you are allergic to aspirin or any other pain reliever/fever reducer

Ask a doctor before use if

- stomach bleeding warning applies to you
- you have a history of stomach problems, such as heartburn
- you have high blood pressure, heart disease, liver cirrhosis, or kidney disease
- you are taking a diuretic
- you have asthma

Ask a doctor or pharmacist before use if you aretaking a prescription drug for:

- diabetes
- gout
- arthritis

Stop use and ask a doctor if

- an allergic reaction occurs. Seek medical help right away.
- you experience any of the following signs of stomach bleeding:
  - feel faint
  - vomit blood
  - have bloody or black stools
  - have stomach pain that does not get better
- pain gets worse or lasts for more than 10 days
- redness or swelling is present
- fever gets worse or lasts for more than 3 days
- new symptoms occur
- ringing in the ears or loss of hearing occurs

These could be signs of a serious condition.

PREGNANCY OR BREAST FEEDING

If pregnant or breast-feeding,ask a health professional before use. It is especially important not to use aspirin during the last 3 months of pregnancy unless definitely directed to do so by a doctor because it may cause problems in the unborn child or complications during delivery.

Keep out of reach of children.In case of overdose, get medical help or contact a Poison Control Center right away (1-800-222-1222).

Directions

- drink a full glass of water with each dose
- adults and children 12 years and over: take 1 or 2 tablets every 4 hours or 3 tablets every 6 hours, not to exceed 12 tablets in 24 hours
- children under 12 years: consult a doctor

Other information

- store between 20°-25°C (68°-77°F) in a dry place
- retain carton for complete product information and warnings

Inactive ingredients

corn starch, croscarmellose sodium, hypromellose, microcrystalline cellulose, mineral oil, titanium dioxide

Questions or comments?

1-844-705-4384

PRINCIPAL DISPLAY PANEL

HyVee®

NDC 42507-018-11

†Compare to the Active Ingredient in Bayer® Aspirin

Regular Strength

Aspirin 325 mg

Pain Reliever/ Fever Reducer (NSAID)

Actual size

100 COATED TABLETS